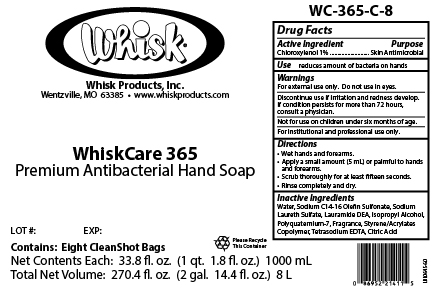 DRUG LABEL: WhiskCare 365
NDC: 65585-365 | Form: SOAP
Manufacturer: Whisk Products, Inc.
Category: otc | Type: HUMAN OTC DRUG LABEL
Date: 20231201

ACTIVE INGREDIENTS: CHLOROXYLENOL 10 mg/1 mL
INACTIVE INGREDIENTS: EDETATE SODIUM; POLYQUATERNIUM-7 (70/30 ACRYLAMIDE/DADMAC; 1600000 MW); SODIUM C14-16 OLEFIN SULFONATE; SODIUM LAURETH SULFATE; LAURIC DIETHANOLAMIDE; ISOPROPYL ALCOHOL; CITRIC ACID MONOHYDRATE

WhiskCare 365

Active Ingredient

Chloroxylenol 1%

Purpose

Skin Antimicrobial

Use

reduces amount of bacteria on hands

Warnings

For external use only. Do not use in eyes.

Discontinue use if irritation and redness develop. If condition persists for more than 72 hours, consult a physician.

KEEP OUT OF REACH OF CHILDREN

Not for use on children under six months of age.

For institutional and professional use only.

Directions

- Wet hands and forearms.
- Apply a small amount (5 mL) or palmful to hands and forearms.
- Scrub thoroughly for at least fifteen seconds.
- Rinse completely and dry.

Inactive Ingredients

Water, Sodium C14-16 Olefin Sulfonate, Sodium Laureth Sulfate, Lauramide DEA, Isopropyl Alcohol, Polyquaternium-7, Fragrance, Styrene/Acrylates Copolymer, Tetrasodium EDTA, Citric Acid